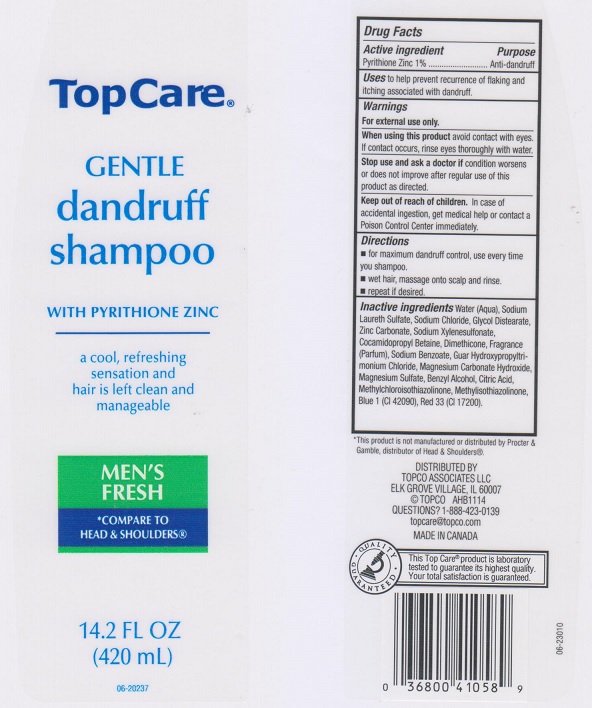 DRUG LABEL: DANDRUFF
NDC: 36800-309 | Form: SHAMPOO
Manufacturer: TOPCO ASSOCIATES LLC
Category: otc | Type: HUMAN OTC DRUG LABEL
Date: 20170620

ACTIVE INGREDIENTS: PYRITHIONE ZINC 1 g/100 mL
INACTIVE INGREDIENTS: WATER; SODIUM LAURETH SULFATE; SODIUM CHLORIDE; GLYCOL DISTEARATE; ZINC CARBONATE; SODIUM XYLENESULFONATE; COCAMIDOPROPYL BETAINE; DIMETHICONE; SODIUM BENZOATE; GUAR HYDROXYPROPYLTRIMONIUM CHLORIDE (1.7 SUBSTITUENTS PER SACCHARIDE); MAGNESIUM CARBONATE HYDROXIDE; MAGNESIUM SULFATE, UNSPECIFIED; BENZYL ALCOHOL; CITRIC ACID MONOHYDRATE; METHYLCHLOROISOTHIAZOLINONE; METHYLISOTHIAZOLINONE; FD&C BLUE NO. 1; D&C RED NO. 33

DRUG FACTS

Active ingredient

Pyrithione zinc 1%

Purpose

Anti-dandruff

Uses

to help prevent recurrence of flaking and itching associated with dandruff.

Warnings

For external use only.

When using this product

avoid contact with eyes. If contact occurs, rinse eyes thoroughly with water.

Stop use and ask a doctor if

condition worsens or does not improve after regular use of this product as directed.

Keep out of reach of children.

In case of accidental ingestion, get medical help or contact a Poison Control Center immediately.

Directions

- for maximum dandruff control, use every time you shampoo.
- wet hair, massage onto scalp and rinse.
- repeat if desired.

Inactive ingredients

Water (Aqua), Sodium Laureth Sulfate, Sodium Chloride, Glycol Distearate, Zinc Carbonate, Sodium Xylenesulfonate, Cocamidopropyl Betaine, Dimethicone, Fragrance (Parfum), Sodium Benzoate, Guar Hydroxypropyltrimonium Chloride, Magnesium Carbonate Hydroxide, Magnesium Sulfate, Benzyl Alcohol, Citric Acid, Methylchloroisothiazolinone, Methylisothiazolinone, Blue 1 (CI 42090), Red 33 (CI 17200).